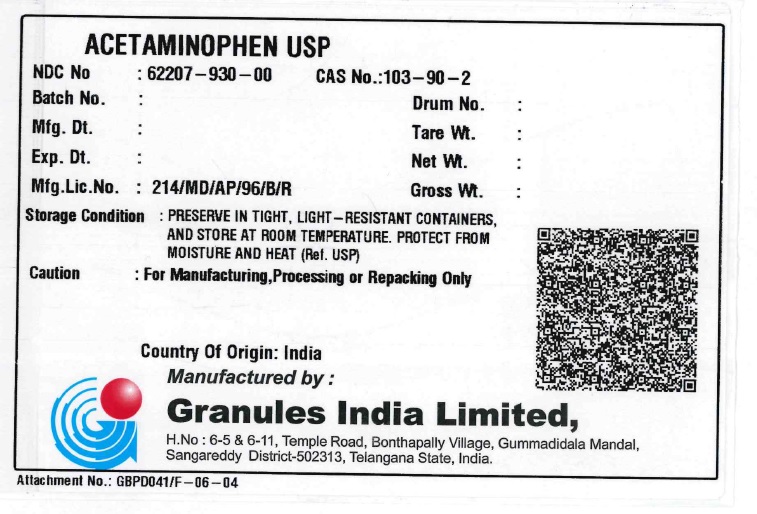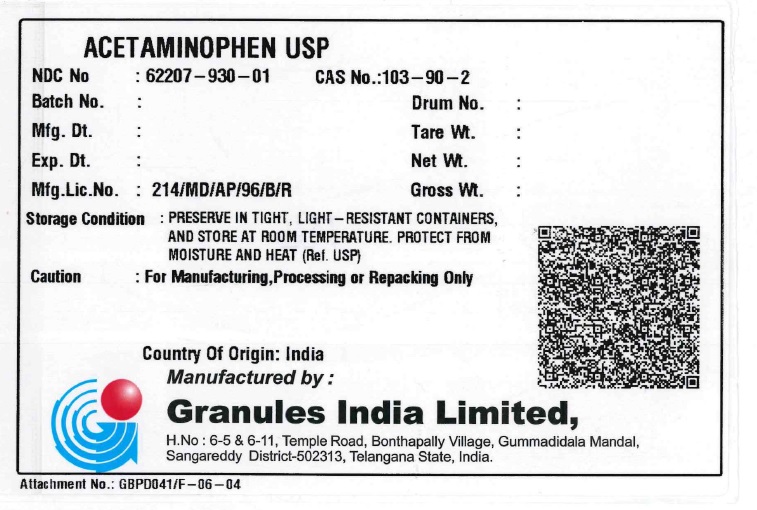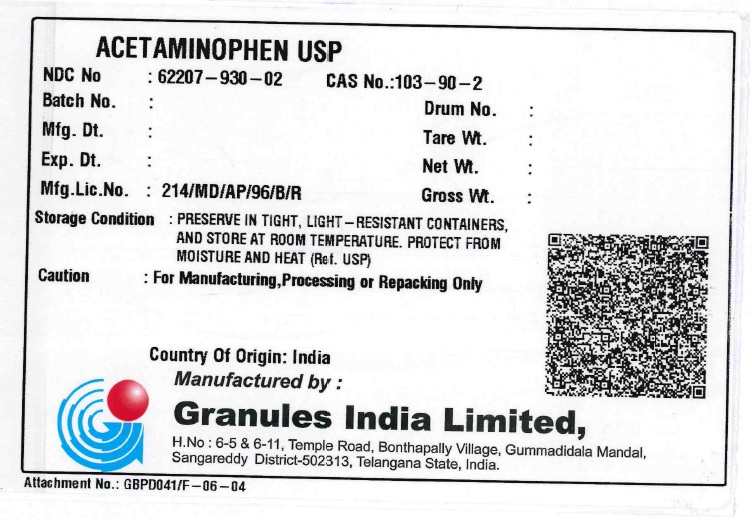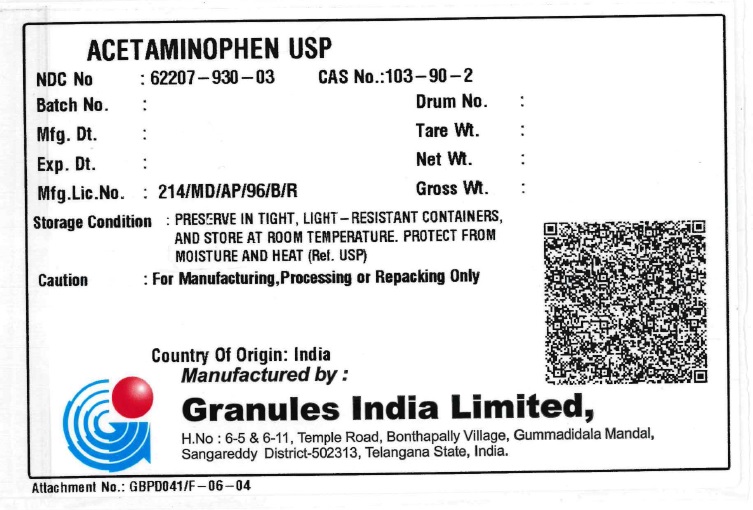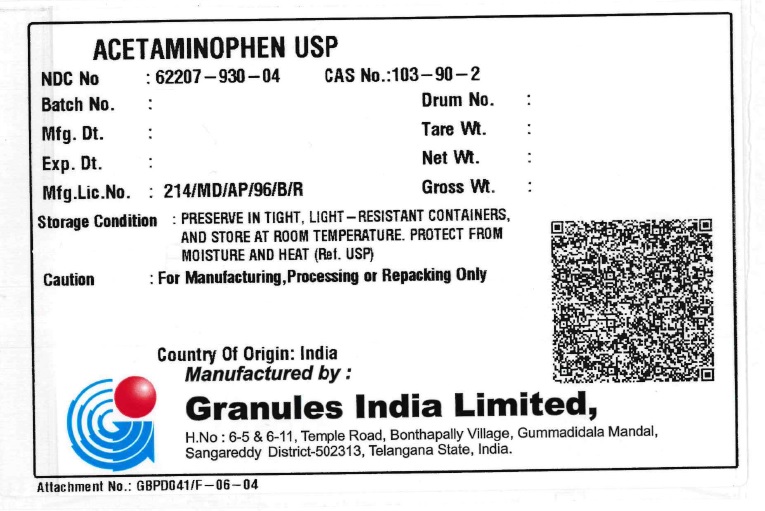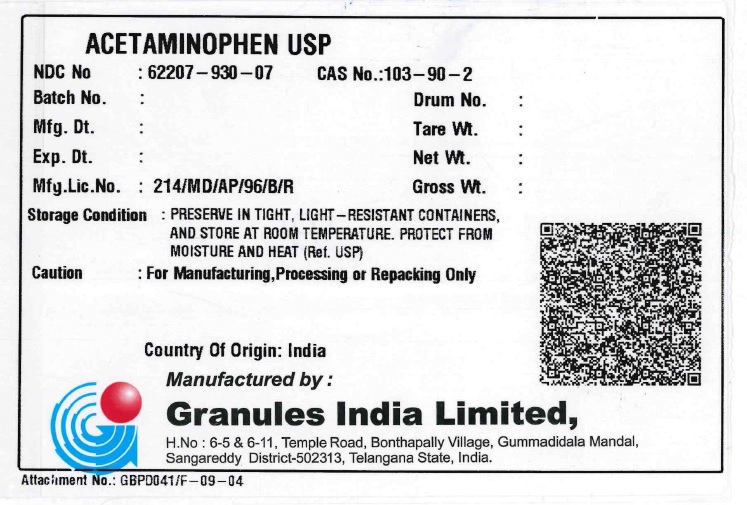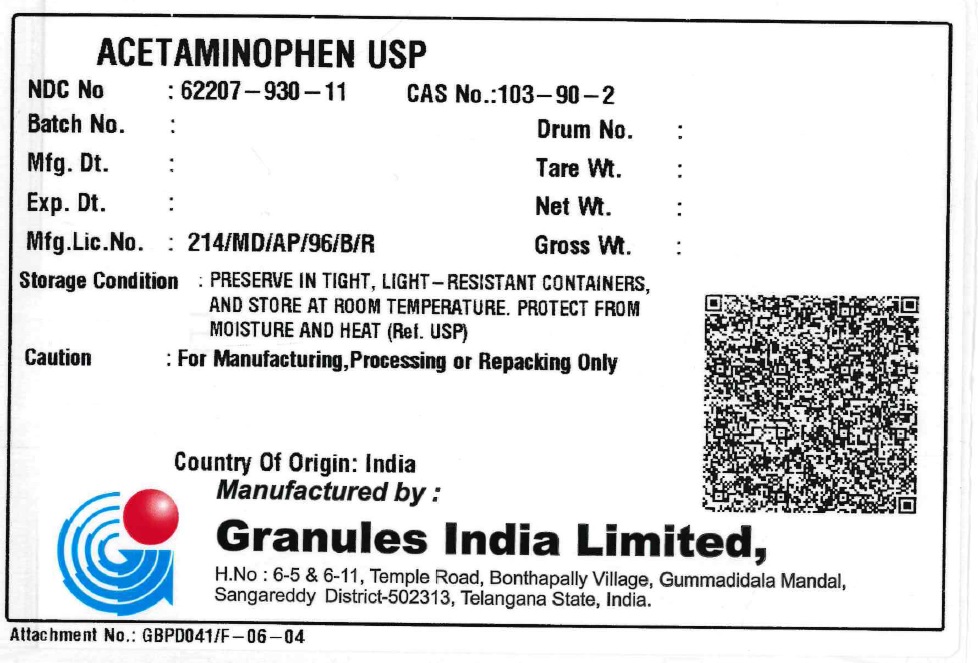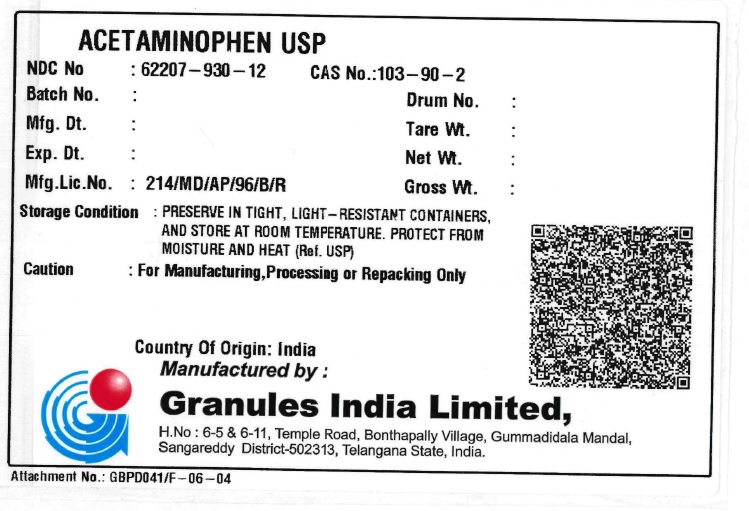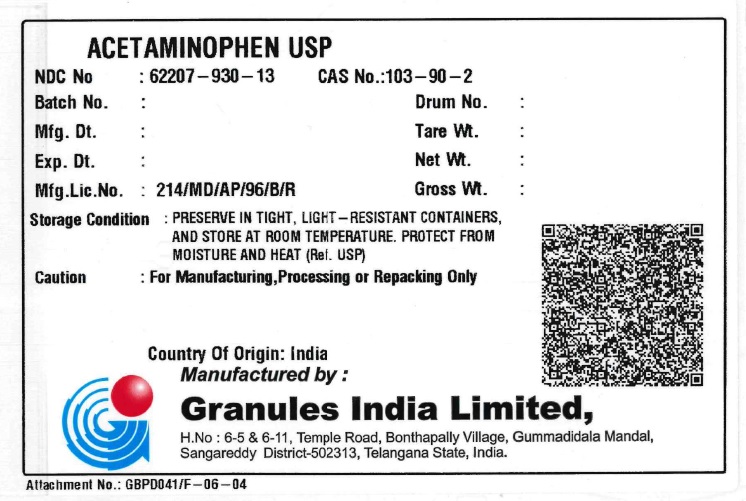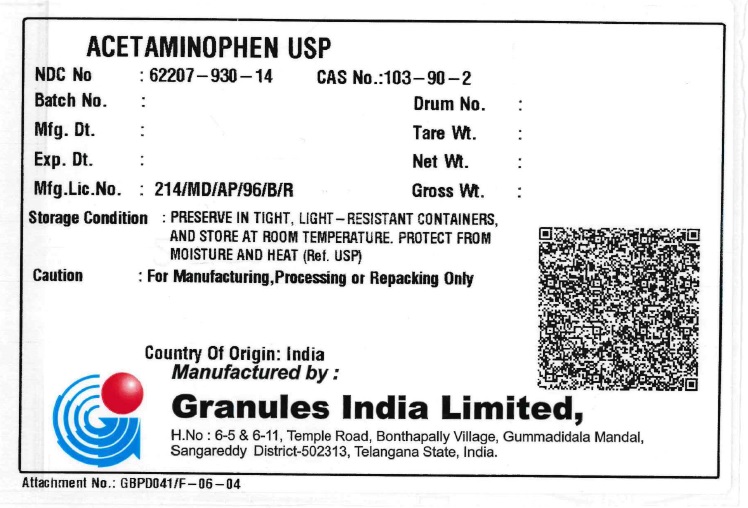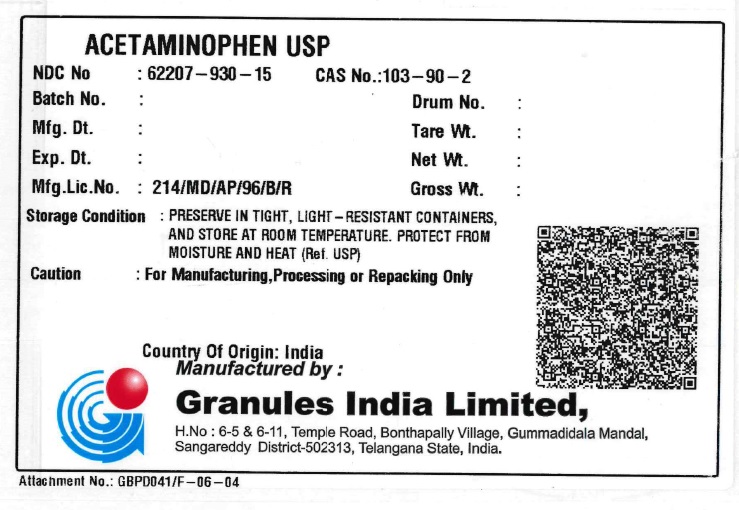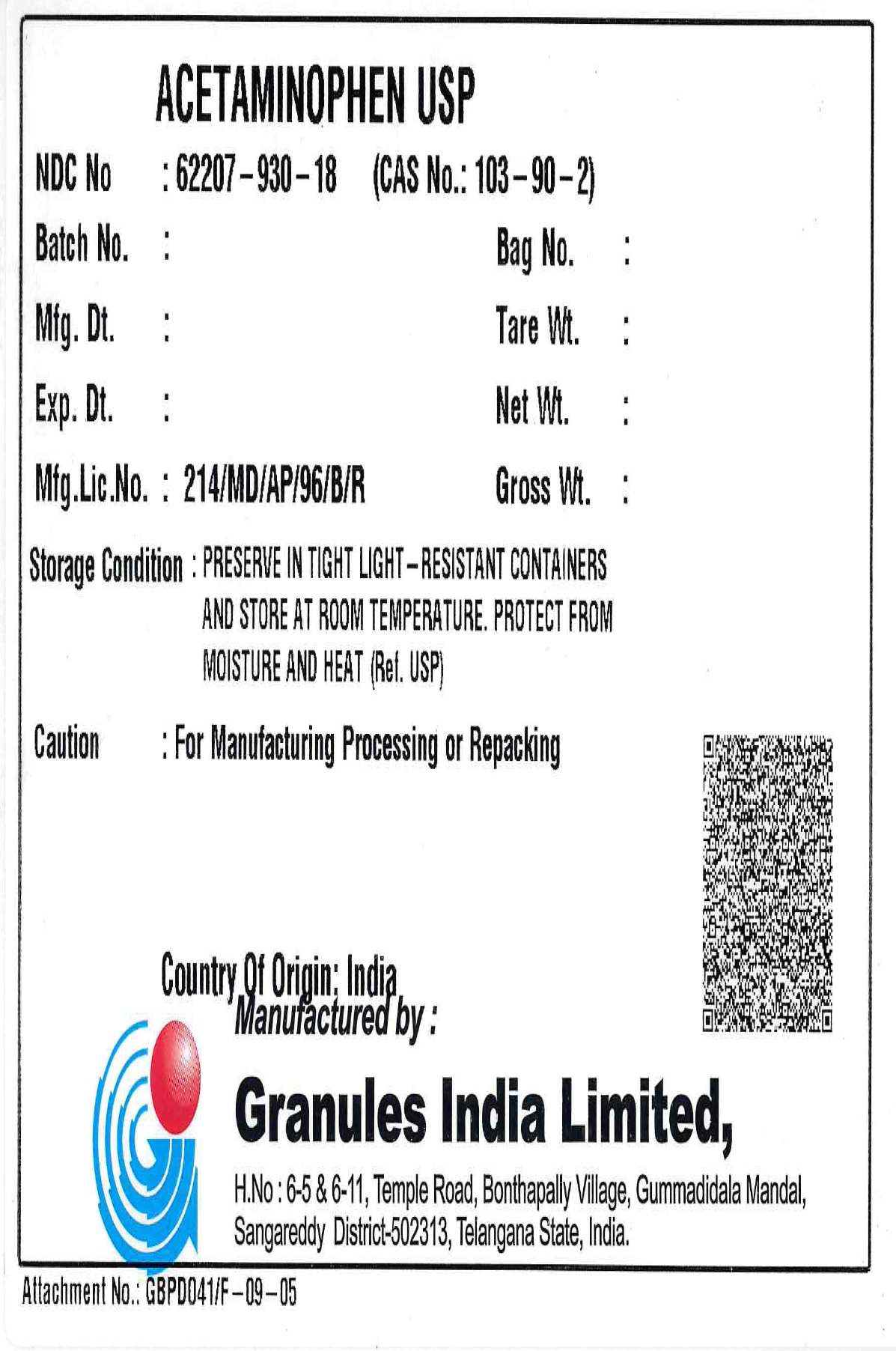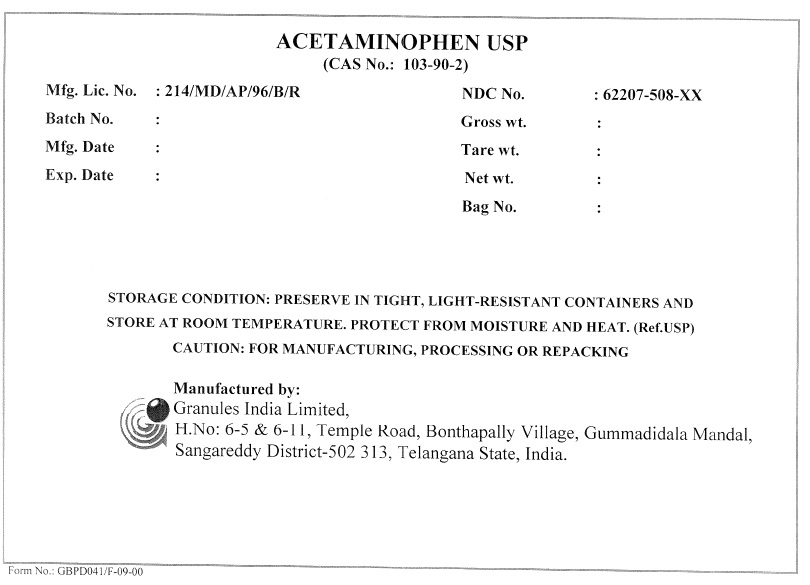 DRUG LABEL: Acetaminophen
NDC: 62207-930 | Form: POWDER
Manufacturer: Granules India Limited
Category: other | Type: BULK INGREDIENT
Date: 20240214

ACTIVE INGREDIENTS: ACETAMINOPHEN 1 kg/1 kg

Acetaminophen USP